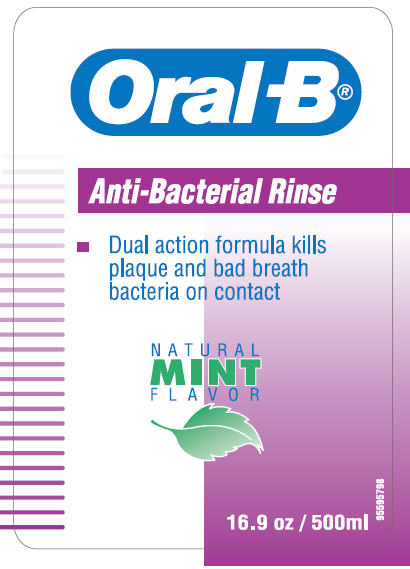 DRUG LABEL: Oral-B
NDC: 0041-1420 | Form: LIQUID
Manufacturer: Oral-B Laboratories
Category: otc | Type: HUMAN OTC DRUG LABEL
Date: 20100402

ACTIVE INGREDIENTS: Cetylpyridinium Chloride 500 ug/1 mL

Oral -B®
Anti-Bacterial Rinse

Drug Facts

Active ingredient

Cetylpyridinium Chloride 0.05%

Purpose

Anti-bacterial

Use

To fight plaque and bad breath bacteria.

Warnings

Keep out of the reach of children.

Not for use by children under six years of age.

Children over six should be supervised when using this product.

Do not use if shrinkband is broken or missing.

WHEN USING

Do not swallow.

Directions

Rinse twice daily, after brushing, with 1/2 a capful (15 ml) for about 30 seconds.

Other information

Store above freezing.

Inactive ingredients

Water, Glycerin, Alcohol (9.3%), Flavor, Poloxamer 407, Methylparaben, Sodium Saccharin, Propylparaben, FD&C Blue #1, and D&C Yellow #10

Question or comments?

1-800-56-ORALB
http://www.oralb.com

Distributed by:
Oral-B, A Division of
Procter & Gamble
Cincinnati, OH 45202

© Oral-B Laboratories

Made in Colombia

PRINCIPAL DISPLAY PANEL - 500ml Label

Oral -B®

Anti-Bacterial Rinse

- Dual action formula kills
  plaque and bad breath
  bacteria on contact

NATURAL
MINT
FLAVOR

16.9 oz / 500ml